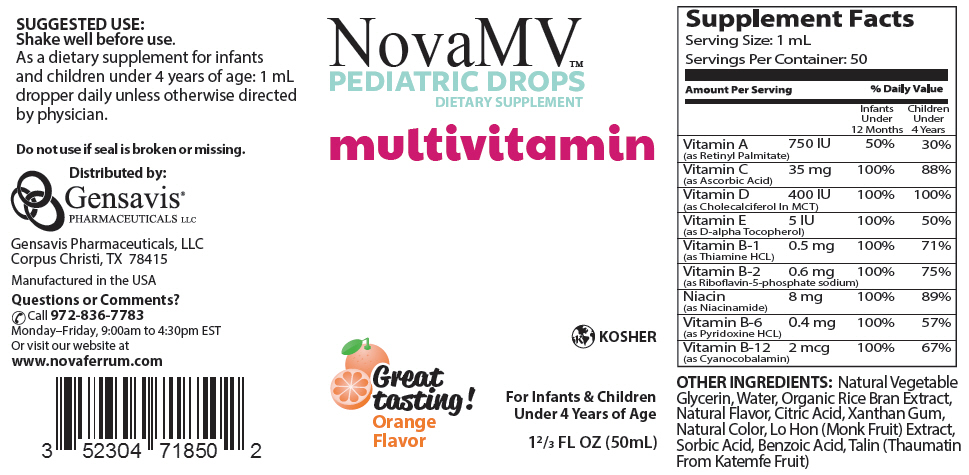 DRUG LABEL: NovaMV 
NDC: 52304-718 | Form: LIQUID
Manufacturer: Gensavis Pharmaceuticals, LLC
Category: other | Type: DIETARY SUPPLEMENT
Date: 20160201

ACTIVE INGREDIENTS: Cyanocobalamin 2 ug/1 mL; Vitamin A 750 [iU]/1 mL; Ascorbic Acid 35 mg/1 mL; Vitamin D 400 [iU]/1 mL; .Alpha.-Tocopherol 5 [iU]/1 mL; Thiamine 0.5 mg/1 mL; Riboflavin 0.6 mg/1 mL; Niacin 8 mg/1 mL; Pyridoxine 0.4 mg/1 mL
INACTIVE INGREDIENTS: Water; Citric Acid Monohydrate; Xanthan Gum; SIRAITIA GROSVENORII FRUIT; Sorbic Acid; Benzoic Acid; Thaumatin

NovaMV™
PEDIATRIC DROPS
DIETARY SUPPLEMENT

STATEMENT OF IDENTITY

Supplement Facts
Serving Size: 1 mL
Servings Per Container: 50
Amount Per Serving |  | % Daily Value
 |  | Infants Under 12 Months | Children Under 4 Years
Vitamin A (as Retinyl Palmitate) | 750 IU | 50% | 30%
Vitamin C (as Ascorbic Acid) | 35 mg | 100% | 88%
Vitamin D (as Cholecalciferol In MCT) | 400 IU | 100% | 100%
Vitamin E (as D-alpha Tocopherol) | 5 IU | 100% | 50%
Vitamin B-1 (as Thiamine HCL) | 0.5 mg | 100% | 71%
Vitamin B-2 (as Riboflavin-5-phosphate sodium) | 0.6 mg | 100% | 75%
Niacin (as Niacinamide) | 8 mg | 100% | 89%
Vitamin B-6 (as Pyridoxine HCL) | 0.4 mg | 100% | 57%
Vitamin B-12 (as Cyanocobalamin) | 2 mcg | 100% | 67%

OTHER INGREDIENTS: Natural Vegetable Glycerin, Water, Organic Rice Bran Extract, Natural Flavor, Citric Acid, Xanthan Gum, Natural Color, Lo Hon (Monk Fruit) Extract, Sorbic Acid, Benzoic Acid, Talin (Thaumatin From Katemfe Fruit)

SUGGESTED USE

Shake well before use.

As a dietary supplement for infants and children under 4 years of age: 1 mL dropper daily unless otherwise directed by physician.

Do not use if seal is broken or missing.

HEALTH CLAIM

Distributed by:
Gensavis Pharmaceuticals, LLC
Corpus Christi, TX 78415
Manufactured in the USA
Questions or Comments?
Call 972-836-7783
Monday–Friday, 9:00am to 4:30pm EST
Or visit our website at
www.novaferrum.com

PRINCIPAL DISPLAY PANEL - 50 mL Bottle Label

NovaMV™
PEDIATRIC DROPS
DIETARY SUPPLEMENT

multivitamin

KOSHER

Great
tasting!
Orange
Flavor

For Infants & Children
Under 4 Years of Age

1⅔ FL OZ (50mL)